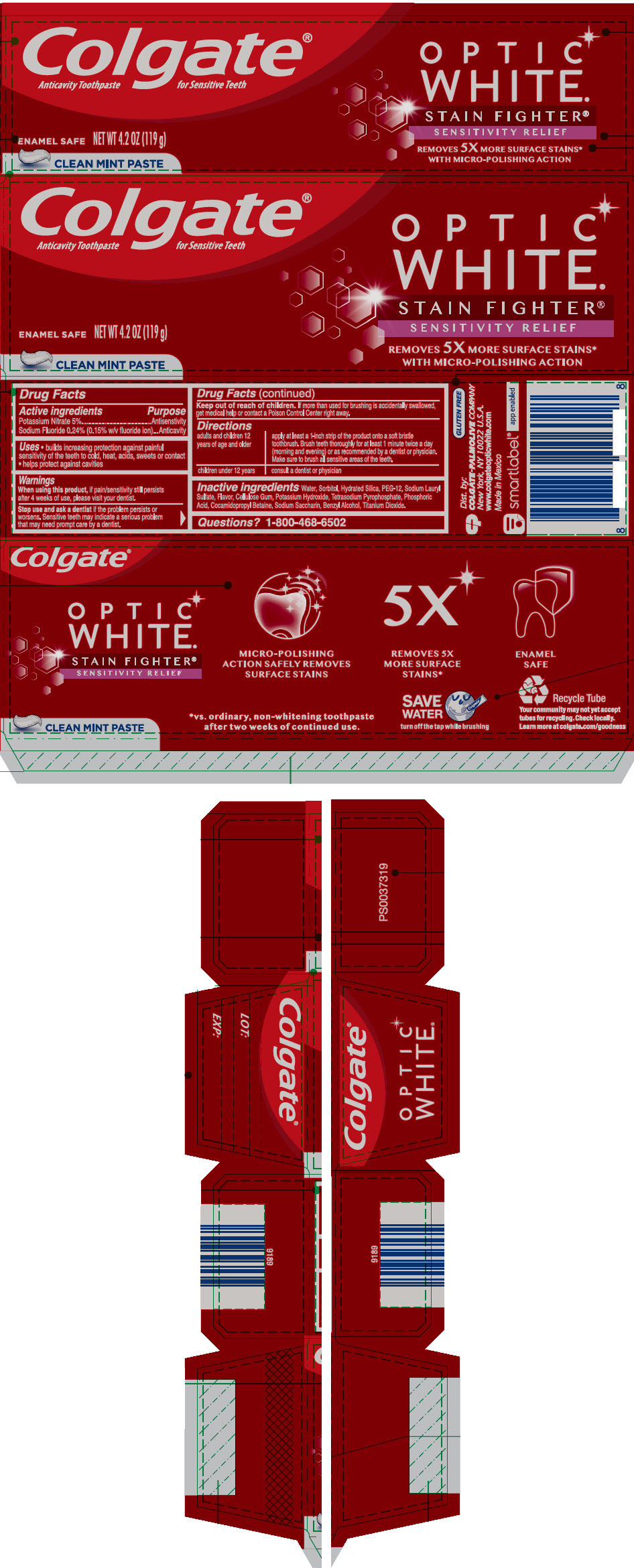 DRUG LABEL: Colgate Optic White Stain Fighter Sens Relief
NDC: 35000-998 | Form: PASTE, DENTIFRICE
Manufacturer: Colgate-Palmolive Company
Category: otc | Type: HUMAN OTC DRUG LABEL
Date: 20240604

ACTIVE INGREDIENTS: SODIUM FLUORIDE 1.5 mg/1 g; POTASSIUM NITRATE 50 mg/1 g
INACTIVE INGREDIENTS: WATER 191.18 mg/1 g; HYDRATED SILICA; SORBITOL; POLYETHYLENE GLYCOL 600; POTASSIUM PYROPHOSPHATE; SODIUM LAURYL SULFATE; CARBOXYMETHYLCELLULOSE; COCAMIDOPROPYL BETAINE; SACCHARIN SODIUM; POTASSIUM HYDROXIDE; TITANIUM DIOXIDE; PHOSPHORIC ACID; BENZYL ALCOHOL

Colgate® Anticavity Toothpaste for Sensitive Teeth OPTIC WHITE® STAIN FIGHTER® SENSITIVITY RELIEF

Drug Facts

ACTIVE INGREDIENT

Active ingredients | Purpose
Potassium Nitrate 5% | Antisenstivity
Sodium Fluoride 0.24% (0.15% w/v fluoride ion) | Anticavity

Uses

- builds increasing protection against painful sensitivity of the teeth to cold, heat, acids, sweets or contact
- helps protect against cavities

Warnings

When using this product, if pain/sensitivity still persists after 4 weeks of use, please visit your dentist.

Stop use and ask a dentist if the problem persists or worsens. Sensitive teeth may indicate a serious problem that may need prompt care by a dentist.

Keep out of reach of children. If more than used for brushing is accidentally swallowed, get medical help or contact a Poison Control Center right away.

Directions

adults and children 12 years of age and older | apply at least a 1-inch strip of the product onto a soft bristle toothbrush. Brush teeth thoroughly for at least 1 minute twice a day (morning and evening) or as recommended by a dentist or physician. Make sure to brush all sensitive areas of the teeth.
children under 12 years | consult a dentist or physician

Inactive ingredients

Water, Sorbitol, Hydrated Silica, PEG-12, Sodium Lauryl Sulfate, Flavor, Cellulose Gum, Potassium Hydroxide, Tetrasodium Pyrophosphate, Phosphoric Acid, Cocamidopropyl Betaine, Sodium Saccharin, Benzyl Alcohol, Titanium Dioxide.

Questions?

1-800-468-6502

Dist. by:
COLGATE-PALMOLIVE COMPANY
New York, NY 10022 U.S.A.

PRINCIPAL DISPLAY PANEL - 119 g Tube Carton

Colgate®

Anticavity Toothpaste for Sensitive Teeth

OPTIC
WHITE®

STAIN FIGHTER®
SENSITIVITY RELIEF

REMOVES 5X MORE SURFACE STAINS*
WITH MICRO-POLISHING ACTION

ENAMEL SAFE

NET WT 4.2 OZ (119 g)

CLEAN MINT PASTE